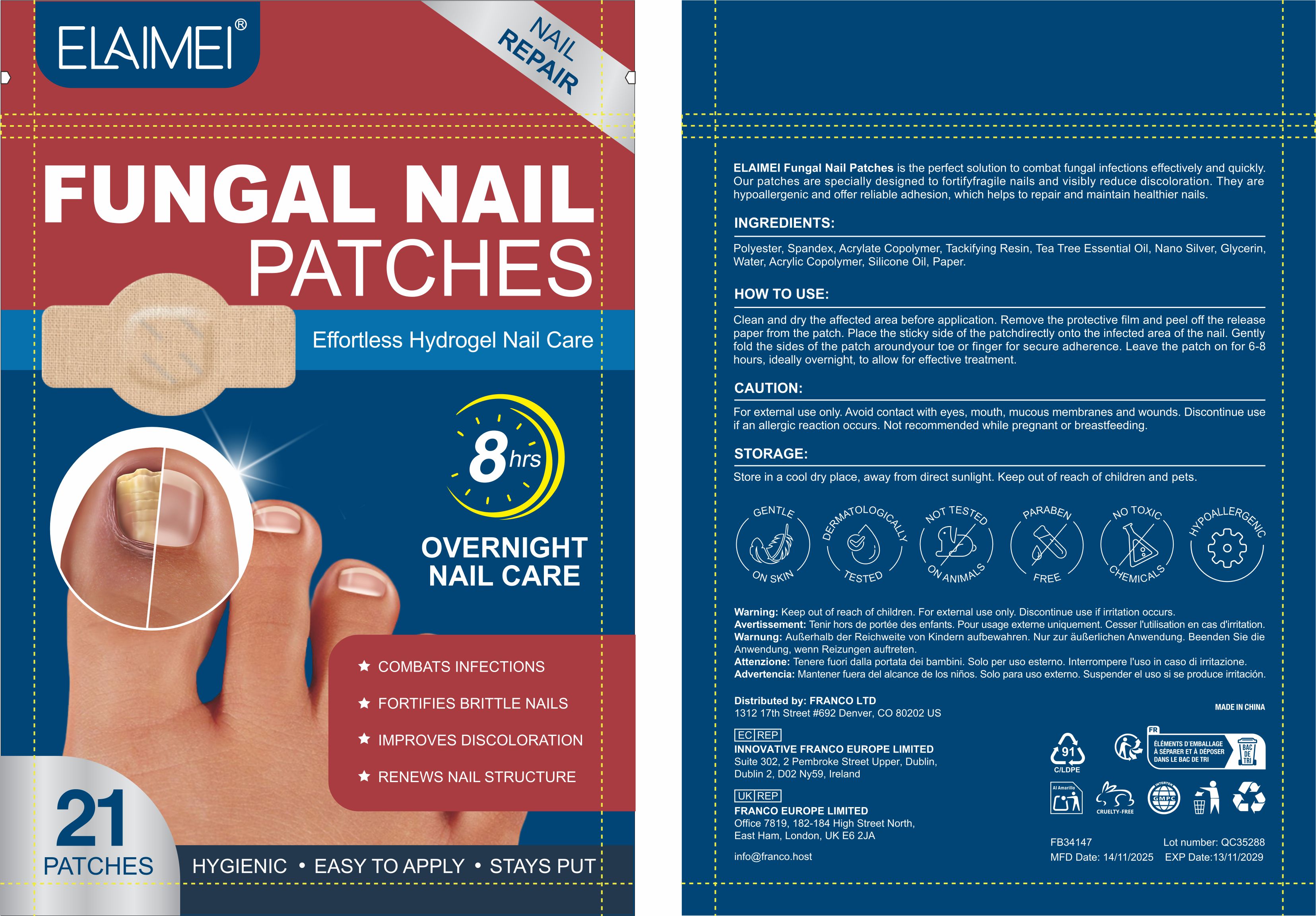 DRUG LABEL: ELAIMEI FUNGAL NAIL PATCHES
NDC: 83804-011 | Form: PATCH
Manufacturer: Shenzhen Shandian Jingling Technology Co., Ltd.
Category: otc | Type: HUMAN OTC DRUG LABEL
Date: 20251210

ACTIVE INGREDIENTS: TEA TREE OIL 0.1 g/1 1
INACTIVE INGREDIENTS: GLYCERIN; POLYESTER-8 (1400 MW, CYANODIPHENYLPROPENOYL CAPPED); WATER

83804-011 ELAIMEI FUNGAL NAIL PATCHES

ACTIVE INGREDIENT

TEA TREE OIL

PURPOSE

antifungal

INDICATIONS AND USAGE

Lofuanna Fungal Nail Patches offers a quick repair solution that works overnight in just 8 hours, Ourpatches are hypoallergenic and specifically designed to fight fungal infections by addressing the rootcause, strengthening brittle nails, and visibly reducing discoloration. The patches are easy to applyand will securely adhere to the nail.

WARNINGS

For external use only.

Not recommended while pregnant or breastfeeding.

WHEN USING

For external use only. Avoid contact with eves, mouth, mucous membranes and wounds. Discontinue use if an allergic reaction occurs. Not recommended while pregnant or breastfeeding.
Store in a cool dry place, away from direct sunlight. Keep out of reach of children and pets

Discontinue use if an allergic reaction occurs.
Discontinue use if irritation occurs

Keep out of reach of children and pets

DOSAGE AND ADMINISTRATION

Clean and dry the affected area before application. Remove the protective film and peel off the releasepaper from the patch. Place the sticky side of the patch directly onto the infected area of the nalil. Gentlyfold the sides of the patch around your toe or finger for secure adherence. Leave the patch on for 6-8hours, ideally overnight, to allow for effective treatment.

INACTIVE INGREDIENT

Polyester
WATER
Glycerin